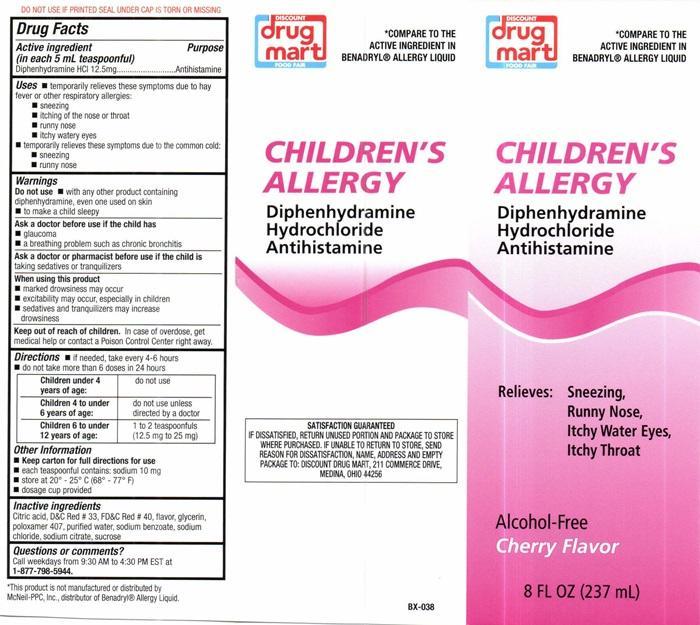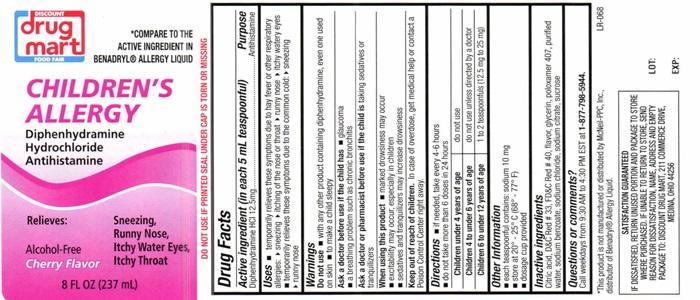 DRUG LABEL: CHILDRENS ALLERGY
NDC: 53943-505 | Form: LIQUID
Manufacturer: Discount Drug Mart
Category: otc | Type: HUMAN OTC DRUG LABEL
Date: 20251219

ACTIVE INGREDIENTS: DIPHENHYDRAMINE HYDROCHLORIDE 12.5 mg/5 mL
INACTIVE INGREDIENTS: ANHYDROUS CITRIC ACID; D&C RED NO. 33; FD&C RED NO. 40; GLYCERIN; POLOXAMER 407; WATER; SODIUM BENZOATE; SODIUM CHLORIDE; SODIUM CITRATE; SUCROSE

Drug Facts Active ingredient (in each 5 mL teaspoonful)

Diphenhydramine HCL 12.5 mg

Purpose

Antihistamine

Keep out of reach of children.In case of overdose, get medical help or contact a Poison Control Center right away.

Uses

- temporarily relieves these symptoms due to hay fever or other respiratory allergies:
- sneezing
- itching of the nose or throat
- runny nose
- itchy watery eyes
- temporarily relieves these symptoms due to the commom cold:
- sneezing
- runny nose

Warnings Do not use

DO NOT USE IF PRINTED SEAL UNDER CAP IS TORN OR MISSING

- with any other product containing didhenhydramine, even one used on skin
- to make a child sleepy

Ask a doctor before use if the child has

- glaucoma
- a breathing problem such as chronic bronchitis

Ask a doctor or pharmacist before use if the child is

taking sedatives or tranquilizers.

When using this product

- marked drowsiness may occur
- excitability may occur, especially in children
- sedatives and tranquilizers may increase drowsiness

Directions

- if needed, take every 4-6 hours
- do not take more than 6 doses in 24 hours

Children under 4 years of age: | do not use
Children 4 to under 6 years of age: | do not use unless directed by a doctor
Children 6 to under 12 years of age: | 1 to 2 teaspoonfuls (12.5 mg to 25 mg)

Other information

- keep carton for full directions for use
- each teaspoonful contains: sodium 10 mg
- store at 20°-25°C (68°-77°F)
- dosage cup provided

Inactive ingredients

Citric acid, D and C Red # 33, FD and C Red # 40, flavor, glycerin, poloxamer 407, purified water, sodium benzoate, sodium chloride, sodium citrate, sucrose

Questions or comments?

Call weekdays from 9:30 AM to 4:30 PM EST at 1-877-798-5944.

DISCOUNT drug mart FOOD FAIR CHILDREN'S ALLERGY product label

* COMPARE TO THE ACTIVE INGREDIENT IN BENADRYL® ALLERGY LIQUID

DISCOUNT drug mart

FOOD FAIR

CHILDREN'S ALLERGY

Diphenhydramine

Hydrochloride

Antihistamine

Relieves: Sneezing

Runny Nose,

Itchy Water Eyes,

Itchy Throat

Alcohol-Free

Cherry Flavor

8 FL OZ (237 mL)

* This product is not manufactured or distributes by Mcneil-PPC, Inc., distributor of Benadryl® Allergy Liquid.

BX-038

SATISFACTION GUARANTEED

IF DISSATISFIED, RETURN UNUSED PORTION AND PACKAGE TO THE STORE WHERE PURCHASED. IF UNABLE TO RETURN TO THE STORE, SEND REASON FOR DISSATISFACTION , NAME, ADDRESS AND EMPTY PACKAGE TO: DISCOUNT DRUG MART, 211 COMMERCE DRIVE MEDINNA, OHIO 44256

res